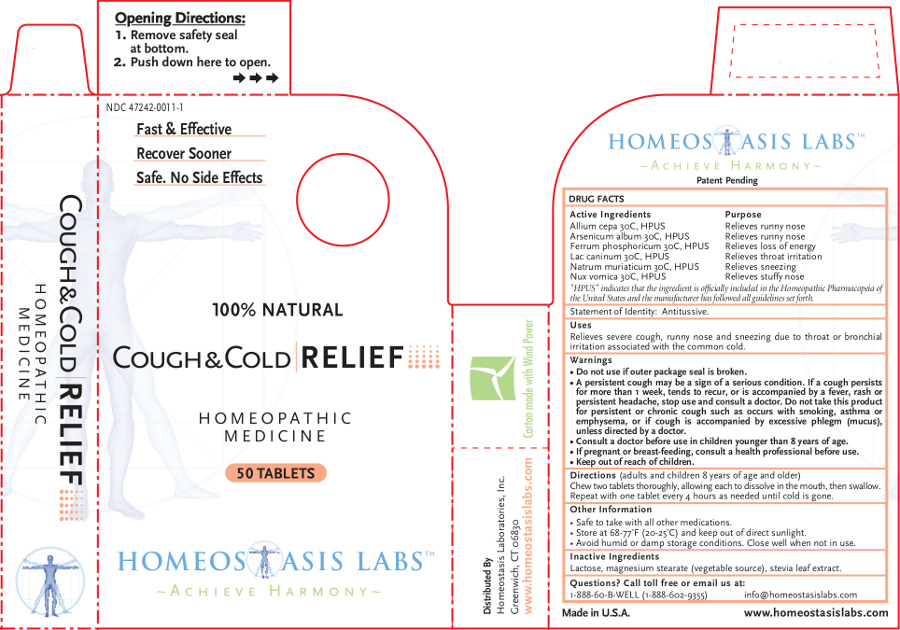 DRUG LABEL: Cough and Cold RELIEF
NDC: 47242-0011 | Form: TABLET, CHEWABLE
Manufacturer: Homeostasis Laboratories, Inc.
Category: homeopathic | Type: HUMAN OTC DRUG LABEL
Date: 20121114

ACTIVE INGREDIENTS: ONION 30 [hp_C]/1 1; ARSENIC TRIOXIDE 30 [hp_C]/1 1; FERROSOFERRIC PHOSPHATE 30 [hp_C]/1 1; CANIS LUPUS FAMILIARIS MILK 30 [hp_C]/1 1; SODIUM CHLORIDE 30 [hp_C]/1 1; STRYCHNOS NUX-VOMICA SEED 30 [hp_C]/1 1
INACTIVE INGREDIENTS: LACTOSE; MAGNESIUM STEARATE; STEVIA REBAUDIUNA LEAF

Cough and Cold RELIEF

Active Ingredients | Purpose
Allium cepa 30C, HPUS | Relieves runny nose
Arsenicum album 30C, HPUS | Relieves runny nose
Ferrum phosphoricum 30C, HPUS | Relieves loss of energy
Lac caninum 30C, HPUS | Relieves throat irritation
Natrum muriaticum 30C, HPUS | Relieves sneezing
Nux vomica 30C, HPUS | Relieves stuffy nose

"HPUS" indicates that the ingredient is officially included in the Homeopathic Pharmacopeia of the United States and the manufacturer has followed all guidelines set forth.

Statement of Identity: Antitussive.

Uses

Relieves severe cough, runny nose and sneezing due to throat or bronchial irritation associated with the common cold.

Warnings

- Do not use if outer package seal is broken.
- A persistent cough may be a sign of a serious condition. If a cough persists for more than 1 week, tends to recur, or is accompanied by a fever, rash or persistent headache, stop use and consult a doctor. Do not take this product for persistent or chronic cough such as occurs with smoking, asthma or emphysema, or if cough is accompanied by excessive phlegm (mucus), unless directed by a doctor.
- Consult a doctor before use in children younger than 8 years of age.

PREGNANCY OR BREAST FEEDING

- If pregnant or breast-feeding, consult a health professional before use.

- Keep out of reach of children.

Directions

(adults and children 8 years of age and older)

Chew two tablets thoroughly, allowing each to dissolve in the mouth, then swallow. Repeat with one tablet every 4 hours as needed until cold is gone.

Other information

- Safe to take with all other medications.
- Store at 68-77°F (20-25°C) and keep out of direct sunlight.
- Avoid humid or damp storage conditions. Close well when not in use.

Inactive Ingredients

Lactose, magnesium stearate (vegetable source), stevia leaf extract.

Questions? Call toll free or email us at:

1-888-60-B-WELL (1-888-602-9355)

info@homeostasislabs.com